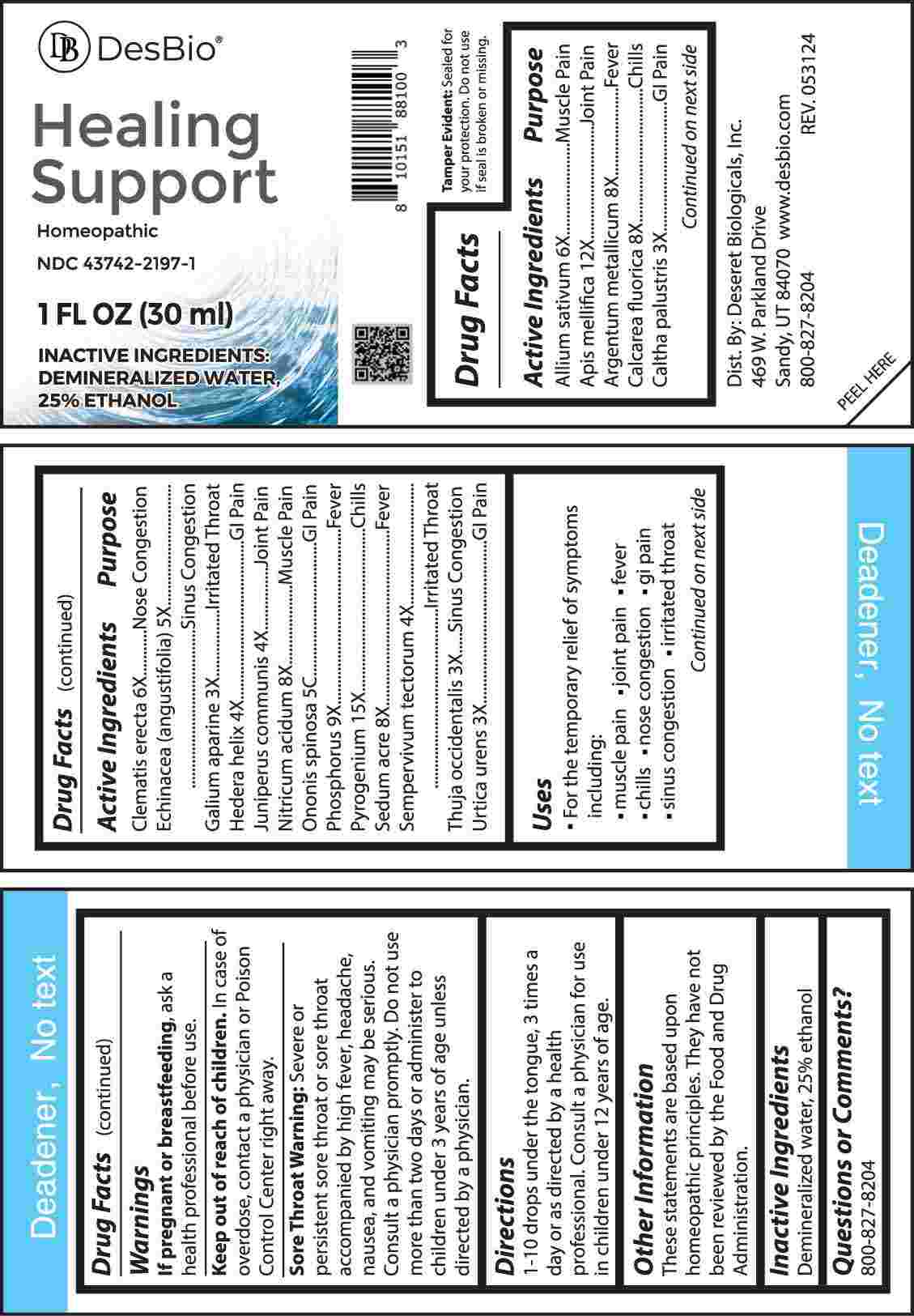 DRUG LABEL: Healing Support
NDC: 43742-2197 | Form: LIQUID
Manufacturer: Deseret Biologicals, Inc.
Category: homeopathic | Type: HUMAN OTC DRUG LABEL
Date: 20240926

ACTIVE INGREDIENTS: GARLIC 6 [hp_X]/1 mL; APIS MELLIFERA 12 [hp_X]/1 mL; SILVER 8 [hp_X]/1 mL; CALCIUM FLUORIDE 8 [hp_X]/1 mL; CALTHA PALUSTRIS WHOLE 3 [hp_X]/1 mL; CLEMATIS RECTA FLOWERING TOP 6 [hp_X]/1 mL; ECHINACEA ANGUSTIFOLIA WHOLE 5 [hp_X]/1 mL; GALIUM APARINE WHOLE 3 [hp_X]/1 mL; HEDERA HELIX FLOWERING TWIG 4 [hp_X]/1 mL; JUNIPER BERRY 4 [hp_X]/1 mL; NITRIC ACID 8 [hp_X]/1 mL; ONONIS SPINOSA WHOLE 5 [hp_C]/1 mL; PHOSPHORUS 9 [hp_X]/1 mL; RANCID BEEF 15 [hp_X]/1 mL; SEDUM ACRE WHOLE 8 [hp_X]/1 mL; SEMPERVIVUM TECTORUM LEAF 4 [hp_X]/1 mL; THUJA OCCIDENTALIS LEAFY TWIG 3 [hp_X]/1 mL; URTICA URENS WHOLE 3 [hp_X]/1 mL
INACTIVE INGREDIENTS: WATER; ALCOHOL

DRUG FACTS:

ACTIVE INGREDIENTS:

Allium Sativum 6X, Apis Mellifica 12X, Argentum Metallicum 8X, Calcarea Fluorica 8X, Caltha Palustris 3X, Clematis Erecta 6X, Echinacea (Angustifolia) 5X, Galium Aparine 3X, Hedera Helix 4X, Juniperus Communis 4X, Nitricum Acidum 8X, Ononis Spinosa 5C, Phosphorus 9X, Pyrogenium 15X, Sedum Acre 8X, Sempervivum Tectorum 4X, Thuja Occidentalis 3X, Urtica Urens 3X

PURPOSE:

Allium Sativum - Muscle Pain, Apis Mellifica – Joint Pain, Argentum Metallicum - Fever, Calcarea Fluorica - Chills, Caltha Palustris – GI Pain, Clematis Erecta – Nose Congestion, Echinacea (Angustifolia) – Sinus Congestion, Galium Aparine – Irritated Throat, Hedera Helix – GI Pain, Juniperus Communis – Joint Pain, Nitricum Acidum – Muscle Pain, Ononis Spinosa – GI Pain, Phosphorus - Fever, Pyrogenium – Chills, Sedum Acre - Fever, Sempervivum Tectorum – Irritated Throat, Thuja Occidentalis – Sinus Congestion, Urtica Urens – GI Pain.

USES:

• For the temporary relief of symptoms including:

• muscle pain • joint pain • fever • chills • nose congestion

gi pain • sinus congestion • irritated throat

These statements are based upon homeopathic principles. They have not been reviewed by the Food and Drug Administration.

WARNINGS:

If pregnant or breast-feeding, ask a health professional before use.

Keep out of reach of children. In case of overdose, contact a physician or Poison Control Center right away.

Sore Throat Warning: Severe or persistent sore throat or sore throat accompanied by high fever, headache, nausea, and vomiting may be serious. Consult a physician promptly. Do not use more than two days or administer to children under 3 years of age unless directed by a physician.

Tamper Evident: Sealed for your protection. Do not use if seal is broken or missing.

KEEP OUT OF REACH OF CHILDREN:

In case of overdose, contact a physician or Poison Control Center right away.

DIRECTIONS:

1-10 drops under the tongue, 3 times a day or as directed by a health professional. Consult a physician for use in children under 12 years of age.

INACTIVE INGREDIENTS:

Demineralized water, 25% ethanol

QUESTIONS:

Dist. By: Deseret Biologicals, Inc.

469 W. Parkland Drive

Sandy, UT 84070

www.desbio.com

800-827-8204

PACKAGE LABEL DISPLAY:

DesBio

Healing Support

Homeopathic

NDC 43742-2197-1

1 FL OZ (30 ml)